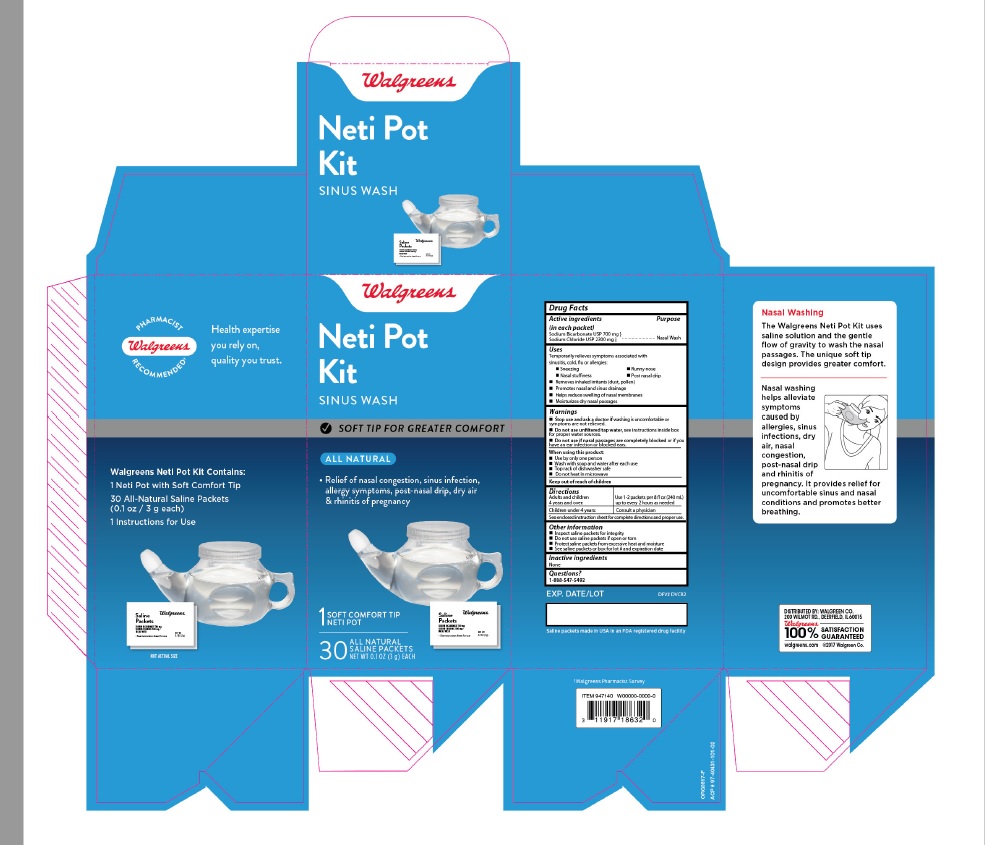 DRUG LABEL: Well at Walgreens
                

NDC: 0363-0504 | Form: KIT | Route: NASAL
Manufacturer: Walgreen Company
Category: otc | Type: HUMAN OTC DRUG LABEL
Date: 20251210

ACTIVE INGREDIENTS: SODIUM CHLORIDE 2300 mg/3000 mg; SODIUM BICARBONATE 700 mg/3000 mg
INACTIVE INGREDIENTS: WATER

Drug Facts

Purpose

Nasal Wash

Uses

Temporarily relieves symptoms associated with

sinusitis, cold, flu or allergies

-Sneezing

-Nasal Stuffiness

-Runny nose

-Post nasal drip

Removes inhaled irritants (dust, pollen)

Removes nasal and sinus drainage

Helps reduce swelling of nasal membranes

Moisturizes dry nasal passages

Keep out of reach of children

Warnings

Stop use and ask a doctor if washing is uncomfortable

or symptoms are not relieved.

Do not use unfiltered tap water. see instructions inside box for proper water sources

Directions

Adults and children 4 years and over: Use 1-2 packets per 8 fl oz (240 mL) up to every two hours as needed.

Children under 4 years: Consult a physician

See enclosed instruction sheet for complete directions and proper use.

Instructions for use

USES:

Temporarily relieves symptoms associated with sinusitis, colds, flu or allergies, including nasal stuffiness, sneezing, runny nose and post-nasal

drip. Removes inhaled irritants (e.g. dust, pollen, smoke). Promotes nasal and sinus drainage. Helps reduce swelling of nasal membranes.

DOSAGE:

Adults and children age 4 years and older may use 1-2 packets of dry ingredients administered as described below as often asd

every 2 hours. For children under age 4 consult a health care professional before use.

DIRECTIONS:

Read through entire section before using for the first time.

1. Remove the cap from the Walgreens Kettle Neti Pot.

2. Pour the pre-mixed saline dry into the Walgreens Kettle Neti Pot. First-time users

should start with one packet of the saline dry ingredients. As you become more accustomed to the system, work up to using 2 full packets,

Additional packets may be purchased from your nearest Walgreens pharmacy.

3. Fill the pot to the 8 oz line with distilled, sterile, or filtered water (using a filter with an absolute pore size of 1 micron or smaller)

or previously boiled (boil water 1 minute or 3 minutes if at elevations above 6,500 feet then allow to cool to body temperature) water.

This makes 1/2 cup (4 oz) of solution.

4. Tighten the cap on the pot securely, place one finger over the spout and one over the hole on the cap and gently shake the pot until

the dry ingredients have completely dissolved.

5. Proper head position allows the solution to run through the nose by gravity.

-Lean over the sink so you are looking directly directly into the basin. Holding the pot in your right hand, gently insert the spout

into your right nostril so that it forms a comfortable seal.

-Rotate your head so that the right nostril is directly above the left. The forehead should remain higher than the chin. Raise the handle of the pot so

that the solution enters the right nostril. In a few moments, the solution will begin to drain out of the right nostril into the sink. Do not inhale or "snort"

solution into the nose - breathe through your mouth.

6. When the pot is empty, exhale through both nostrils to clear them of excess mucous and solution. Gently blow your nose into a tissue.

7. Repeat the procedure on the other side.

8. Thoroughly rinse the pot after each use with water that has been distilled, sterilized, filtered or previously boiled and leave the pot to air dry completely.

The Walgreens Kettle Neti Pot is top-rack dishwasher safe.

Active ingredients

(in each packet)

Sodium Bicarbonate USP (700 mg)

Sodium Chloride USP (2300 mg)

Inactive Ingredients

None